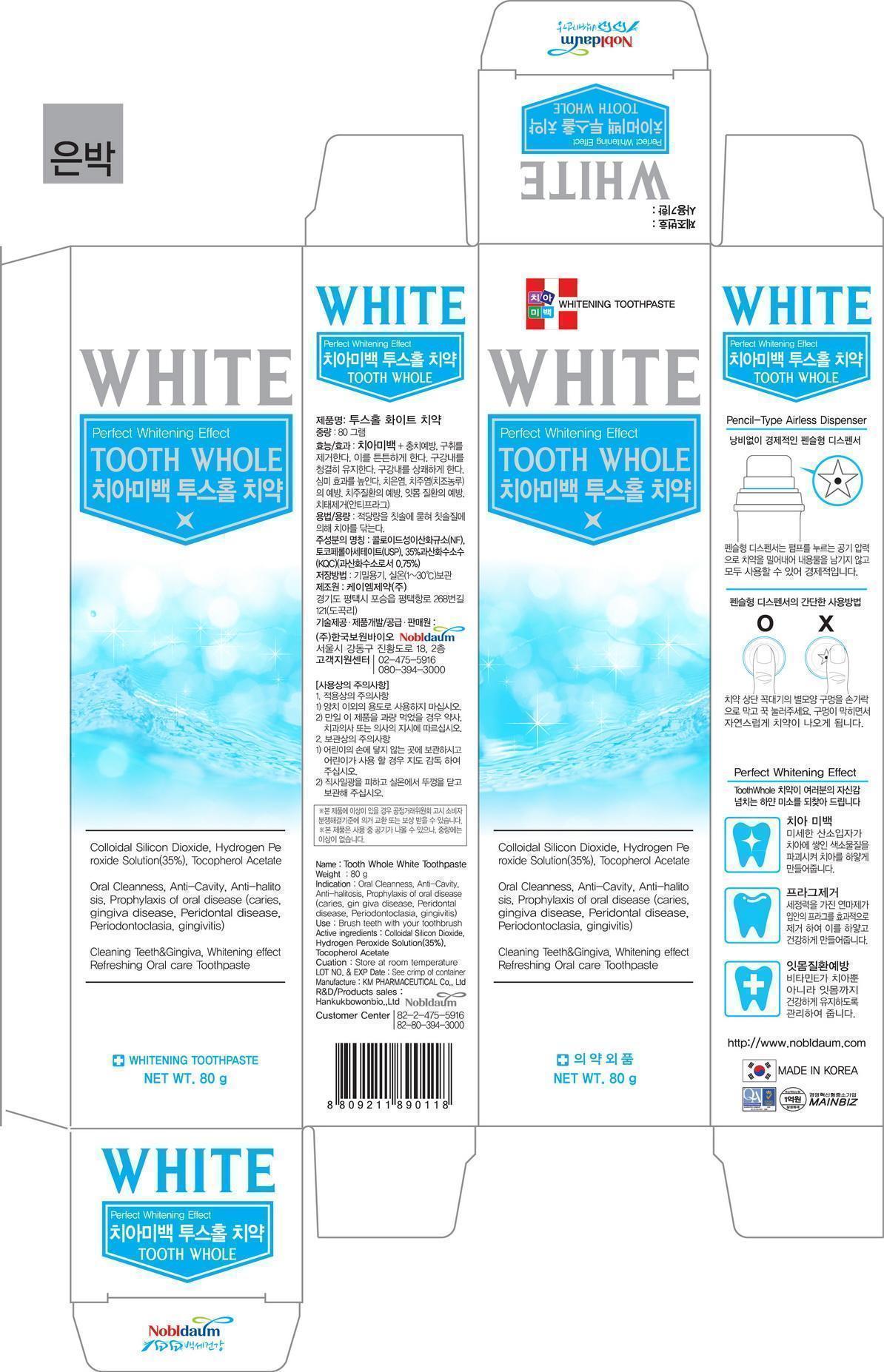 DRUG LABEL: Tooth Whole White
NDC: 60319-5001 | Form: PASTE, DENTIFRICE
Manufacturer: Hankuk Bowonbio Co., Ltd
Category: otc | Type: HUMAN OTC DRUG LABEL
Date: 20191205

ACTIVE INGREDIENTS: HYDROGEN PEROXIDE 2.14 g/100 g
INACTIVE INGREDIENTS: SORBITOL; XYLITOL

Drug Facts

active ingredient: xylitol

INACTIVE INGREDIENT

cetylpyridinium chloride, lactose monohydrate, corn starch, d-sorbitol, ubidecarenone, glycyrrhizae extract, tea chatechin, hydroxyapatite, propolis extract, menthol powder, spirulina color

PURPOSE

whiten and strong teeth
removal of bad breath
prevention of gingivitis and periodontitis
prevention of periodontal diseases and gum diseases
removal of dental plaque

keep out of reach of the children

INDICATIONS AND USAGE

apply Proper Amount of the toothpaste on the tooth.

WARNINGS

■ For tooth only.
■ Avoid contact with eyes.
■ Do not swallow. If swallowed, get medical help.

DOSAGE AND ADMINISTRATION

brush your teeth by putting appropriate amount of powder